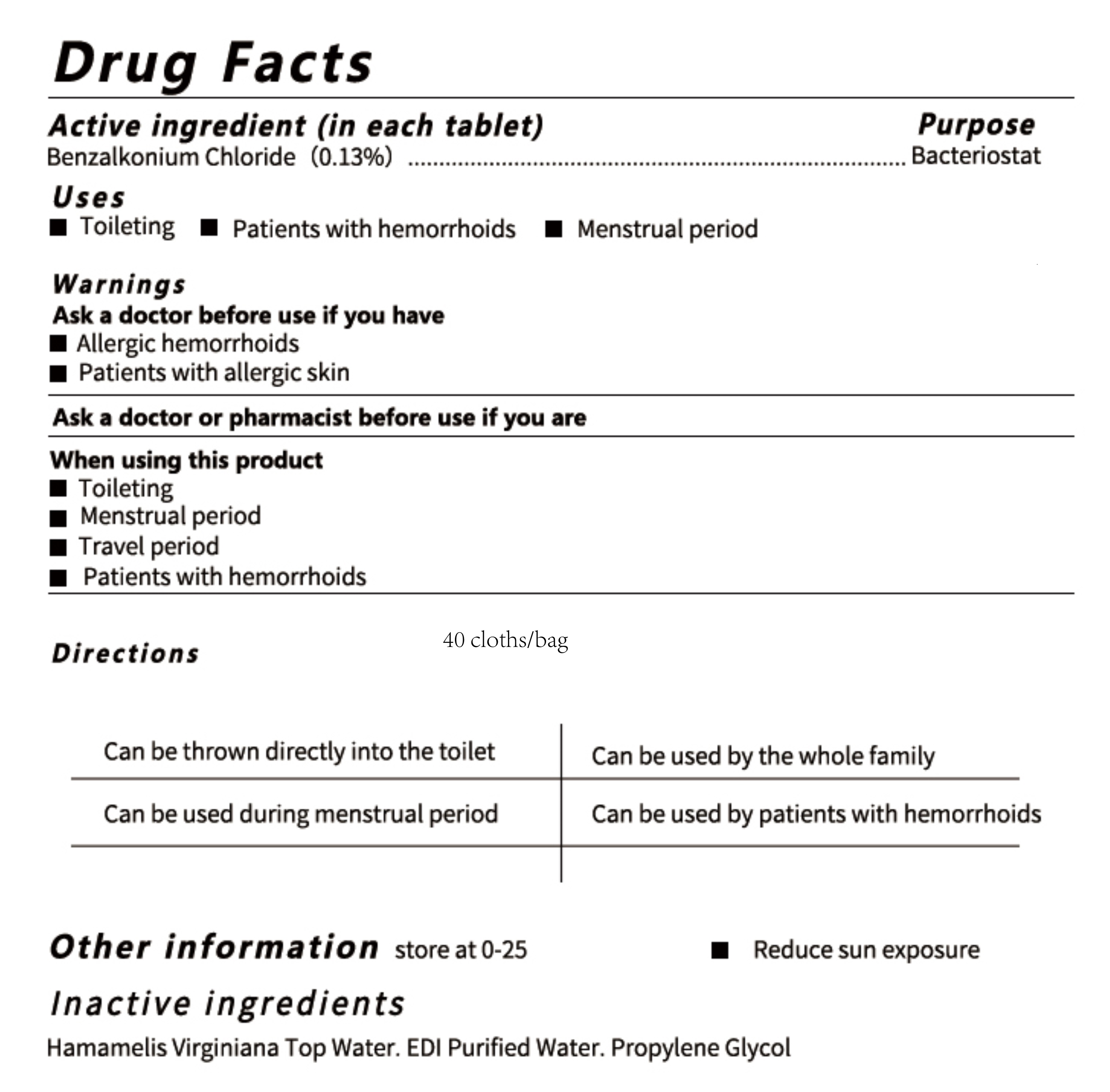 DRUG LABEL: Disinfecting wet wipes
NDC: 81855-001 | Form: CLOTH
Manufacturer: JIANGSU DOUBLECOTTON  CO.,LTD
Category: otc | Type: HUMAN OTC DRUG LABEL
Date: 20210425

ACTIVE INGREDIENTS: BENZALKONIUM CHLORIDE 0.13 g/100 1
INACTIVE INGREDIENTS: HAMAMELIS VIRGINIANA TOP WATER; PROPYLENE GLYCOL; WATER

81855-001
Disinfecting wet wipes

Active Ingredient(s)

Benzalkonium Chloride(0.13%)

Purpose

Bacteriostat

Use

ToiletingPatients with hemorrhoids

Warnings

Ask a doctor before use if you have
Allergic hemorrhoids
Patients with allergic skin

Do not use

/

Ask a doctor or pharmacist before use if you are
When using this product
Toileting
Menstrual period
Travel period
Patients with hemorrhoids

STOP USE

/

KEEP OUT OF REACH OF CHILDREN

/

Directions

Can be thrown directly into the toilet
Can be used by the whole family
Can be used during menstrual period
Can be used by patients with hemorrhoids

Other information

store at 0-25
Reduce sun exposure

Inactive ingredients

Hamamelis Virginiana Top Water. EDI Purified Water. Propylene Glycol

Package Label - Principal Display Panel

81855-001-01 40CLOTH IN 1BAG